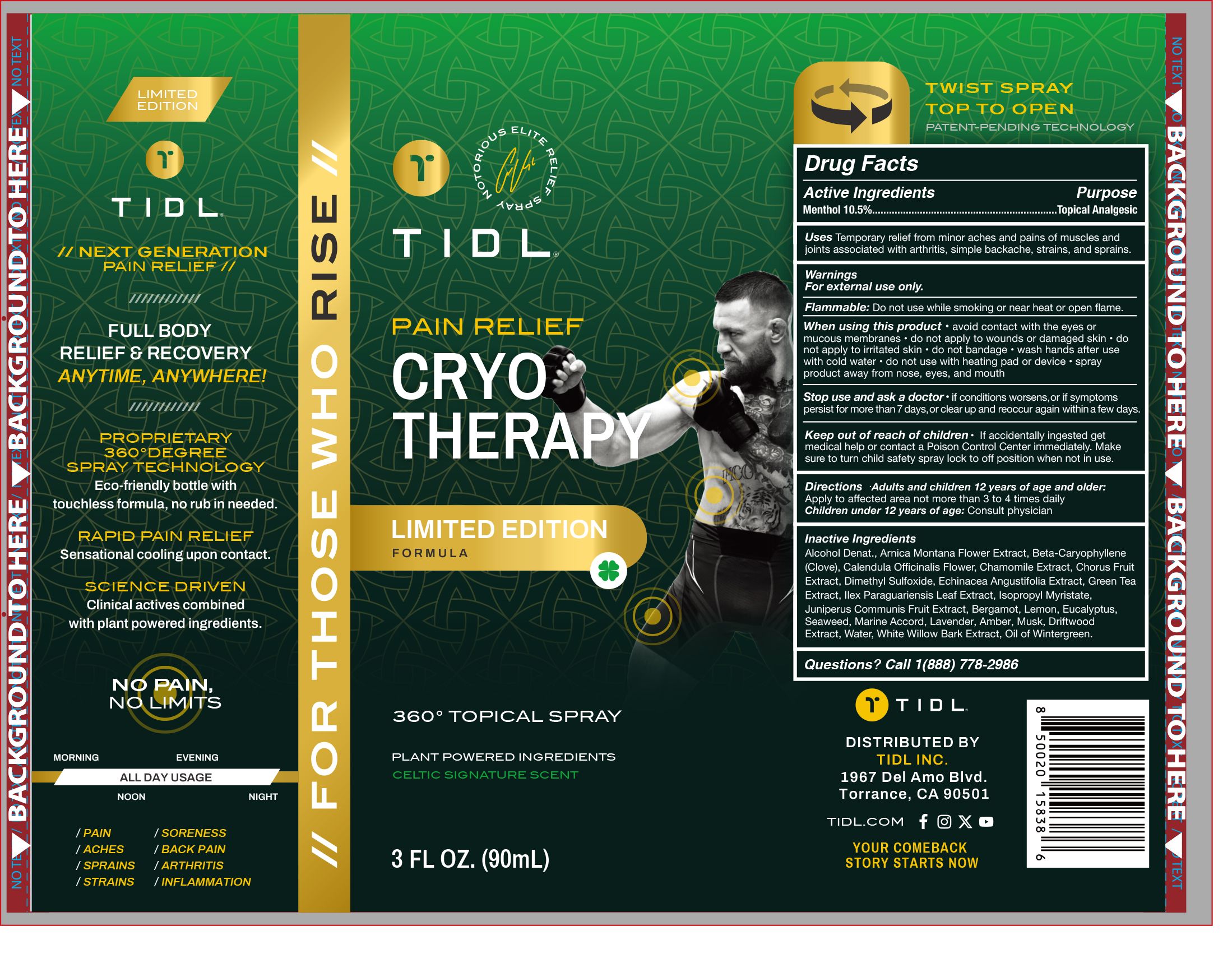 DRUG LABEL: TIDL Pain Relief CRYO Therapy Limited Edition
NDC: 84214-008 | Form: SPRAY
Manufacturer: Shenzhen Sam Technology Co., Ltd.
Category: otc | Type: HUMAN OTC DRUG LABEL
Date: 20240719

ACTIVE INGREDIENTS: MENTHOL 10.5 g/100 mL
INACTIVE INGREDIENTS: CHAMOMILE; ALCOHOL; ILEX PARAGUARIENSIS LEAF; JUNIPER BERRY; AMBER; LEMON; LAVANDULA ANGUSTIFOLIA FLOWER; OXACYCLOHEPTADEC-8-EN-2-ONE, (8Z)-; CALENDULA OFFICINALIS FLOWER; ECHINACEA ANGUSTIFOLIA; CARYOPHYLLENE; GREEN TEA LEAF; CUCURBITACIN B; ISOPROPYL MYRISTATE; NORI; EUCALYPTUS GUM; DIMETHYL SULFOXIDE; ARNICA MONTANA FLOWER; INULA RACEMOSA ROOT; METHYL SALICYLATE; WATER; CITRUS FRUIT; SALIX ALBA BARK; BERGAMOT OIL

84214-008

Active Ingredient

Menthol 10.5%

Purpose

Topical Analgesic

Use

Temporary relief from minor aches and pains of muscles and joints associated with arthritis，simple backache，strains and sprains

Warnings

For external use only

Do not use

While smoking or near heat or open flame

When Using

·avoid contact with the eyes or mucous membranes
·do not apply to wounds or damaged skin
·do not apply to irritated skin
·do not bandage
·wash hands after use with cool water
·do not use with heating pad or device
·spray product away from nose,eyes,and mouth

Stop Use

if condition worsens, or if symptoms persist for more than 7 days, or clear up and reoccur again within a few days

Ask Doctor

if condition worsens, or if symptoms persist for more than 7 days, or clear up and reoccur again within a few days

Keep Oot Of Reach Of Children

If accidentally ingested get medical help or contact a Poison Control Center immediately. Make sure to turn child safety spray lock to off position when not in use.

Directions

·Adults and children 12 years of age and older：Apply to affected area not more than 3 to 4 times daily
·Children under 12 years of age：Consult physician

Inactive ingredients

Alcohol Denat, Arnica Montana Flower Extract, Beta-Caryophyllene（Clove）, Calendula Officinalis Flower, Chamomile Extract, Chorus Fruit Extract，Dimethyl Sulfoxide, Echinacea Angustifolia Extract, Green Tea Extract，Ilex Paraguariensis Leaf Extract, Isopropyl Myristate, Juniperus Communis Fruit Extract, Bergamot，Lemon，Eucalyptus，Seaweed，Marine Accord，Lavender，Amber，Musk，Driftwood Extract，Water, White Willow Bark Extract, Oil of Wintergreen.

Questions

Call 1(888) 778-2986